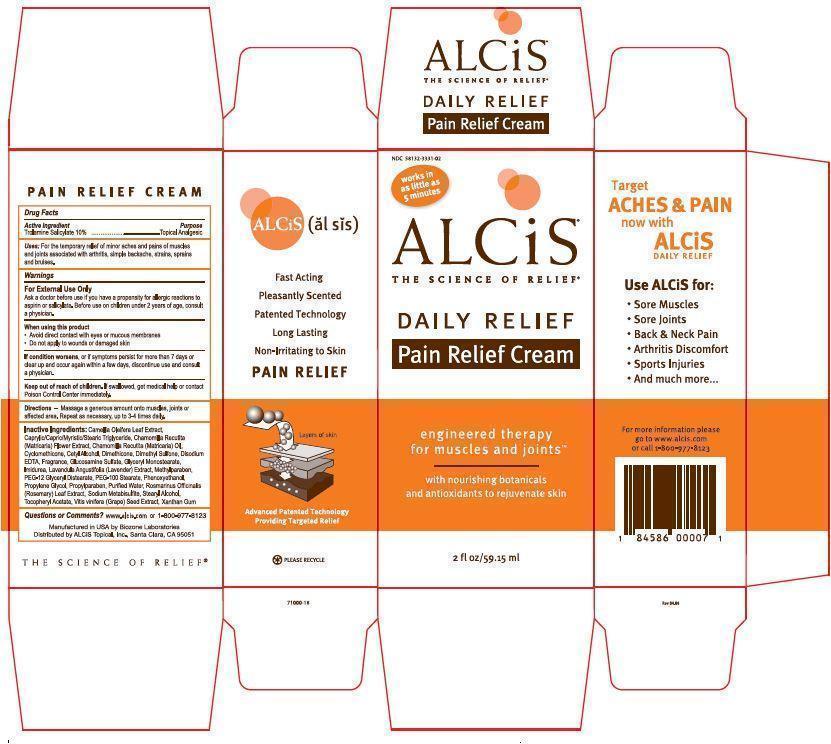 DRUG LABEL: Alcis Daily Relief Pain Relief
NDC: 58132-3331 | Form: CREAM
Manufacturer: Alcis Topical, Inc.
Category: otc | Type: HUMAN OTC DRUG LABEL
Date: 20130628

ACTIVE INGREDIENTS: TROLAMINE SALICYLATE 10 g/100 mL
INACTIVE INGREDIENTS: CAMELLIA OLEIFERA LEAF; MEDIUM-CHAIN TRIGLYCERIDES; CHAMOMILE; CYCLOMETHICONE; CETYL ALCOHOL; DIMETHICONE; DIMETHYL SULFONE; EDETATE DISODIUM; GLUCOSAMINE SULFATE; GLYCERYL MONOSTEARATE; IMIDUREA; LAVANDULA ANGUSTIFOLIA FLOWERING TOP; METHYLPARABEN; POLYETHYLENE GLYCOL 600; GLYCERYL DISTEARATE; PEG-100 STEARATE; PHENOXYETHANOL; PROPYLENE GLYCOL; PROPYLPARABEN; WATER; ROSEMARY; SODIUM METABISULFITE; STEARYL ALCOHOL; .ALPHA.-TOCOPHEROL ACETATE; VITIS VINIFERA SEED; XANTHAN GUM

Drug Facts

Active ingredients
Trolamine Salicylate 10%

Purpose
Topical Analgesic

INDICATIONS AND USAGE

Uses: For the temporary relief of minor aches and pains of muscles and joints associated with arthritis, simple backache, strains, sprains and bruises.

Warnings

For External Use Only

Ask a doctor before use if you have a propensity for allergic reactions to aspirin or salicylate. Before use on children under 2 years of age, consult a physician.

When using this product

- Avoid direct contact with eyes or mucous membranes
- Do not apply to wounds or damaged skin

STOP USE

If condition worsens, or if symptoms persist for more than 7 days or clear up and occur again within a few days, discontinue use and consult a physician.

Keep out of reach of children. If swallowed, get medical help or contact Poison Control Center Immediately.

DOSAGE AND ADMINISTRATION

Directions-Massage a generous amount onto muscles, joints or affected area. Repeat as necessary, up to 3-4 times daily.

INACTIVE INGREDIENT

Inactive Ingredients: Camellia oleifera Leaf Extract, Caprylic/Capric/Myristic/Stearic Triglyceride, Chamomilla recutita (Matricaria) Flower Extract, Chamomilla recutita (Matricaria) Oil, Cyclomethicone, Cetyl Alcohol, Dimethicone, Dimethyl Sulfone, Disodium EDTA, Fragrance, Glucosamine Sulfate, Glyceryl Monostearate, Imidurea, Lavandula angustifol (lavender) Extract, Methylparaben, PEG-12 Glyceryl Distearate, PEG-100 Stearate, Phenoxyethanol, Propylene Glycol, Propylparaben, Purified Water, Rosmarinus officinalis (Rosemary) Oil, Sodium Metabisulfite, Stearyl Alcohol, Tocopheryl Acetate, Vitis vinifera (Grape) Seed Extract, Xanthan Gum

Questions or comments? 1-800-977-8123
www.alcis.com

Manufactured in USA by Biozone Laboratories
Distributed by ALCiS Topical, Inc., Santa Clara, CA 95051 Rev.

PRINCIPAL DISPLAY PANEL - 88.7 mL container

NDC 58132-3331-02

works in as little as 5 minutes

ALCiS®
THE SCIENCE OF RELIEF®

DAILY RELIEF

PAIN RELIEF CREAM

engineered therapy
for muscles and jointsTM

with nourishing botanicals
and antioxidants to rejuvenate skin

2 fl oz / 59.15 ml

Manufactured in USA by Biozone Laboratories
Distributed by ALCiS Topical, Inc., Santa Clara, CA 95051 Rev.